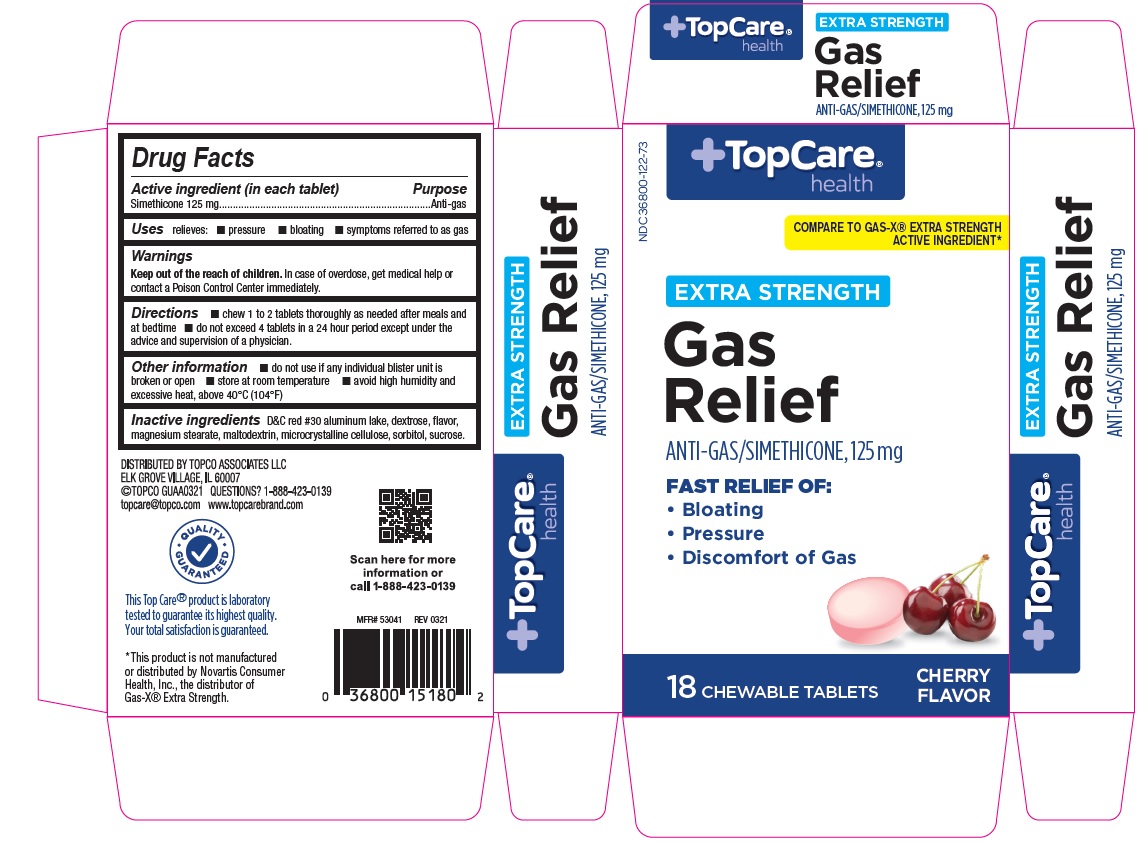 DRUG LABEL: Gas Relief
NDC: 36800-122 | Form: TABLET, CHEWABLE
Manufacturer: Topco Associates, LLC
Category: otc | Type: Human OTC Drug Label
Date: 20241226

ACTIVE INGREDIENTS: DIMETHICONE 125 mg/1 1
INACTIVE INGREDIENTS: D&C RED NO. 30; MAGNESIUM STEARATE; CELLULOSE, MICROCRYSTALLINE; SORBITOL; SUCROSE; MALTODEXTRIN; DEXTROSE, UNSPECIFIED FORM

Topco Extra Strength Gas Relief Tablets

ACTIVE INGREDIENT(in each tablet)

Simethicone 125 mg

PURPOSE

Anti-gas

USE(S)

relieves:

- pressure
- bloating
- symptoms referred to as gas

WARNINGS

.

KEEP OUT OF REACH OF CHILDREN

In case of overdose, get medical help or contact a poison control center immediately.

DIRECTIONS

- chew 1 to 2 tablets thoroughly as needed after meals and at bedtime
- do not exceed 4 tablets in a 24 hour period except under the advice and supervision of a physician

OTHER INFORMATION

- do not use if any individual blister unit is broken or open
- store at room temperature
- avoid high humidity and excessive heat, above 40ºC (104ºF)

INACTIVE INGREDIENTS

D&C red # 30 aluminum lake, dextrose, flavor, magnesium stearate, maltodextrin, microcrystalline cellulose, sorbitol, sucrose

PRINCIPAL DISPLAY PANEL

Topcare
NDC 36800-122-73
COMPARE TO GAS-X® EXTRA STRENGTH ACTIVE INGREDIENT*
EXTRA STRENGTH
Gas
Relief
ANTI-GAS/SIMETHICONE, 125 mg
FAST RELIEF OF:

- Bloating
- Pressure
- Discomfort of Gas

CHERRY FLAVOR

18 CHEWABLE TABLETS